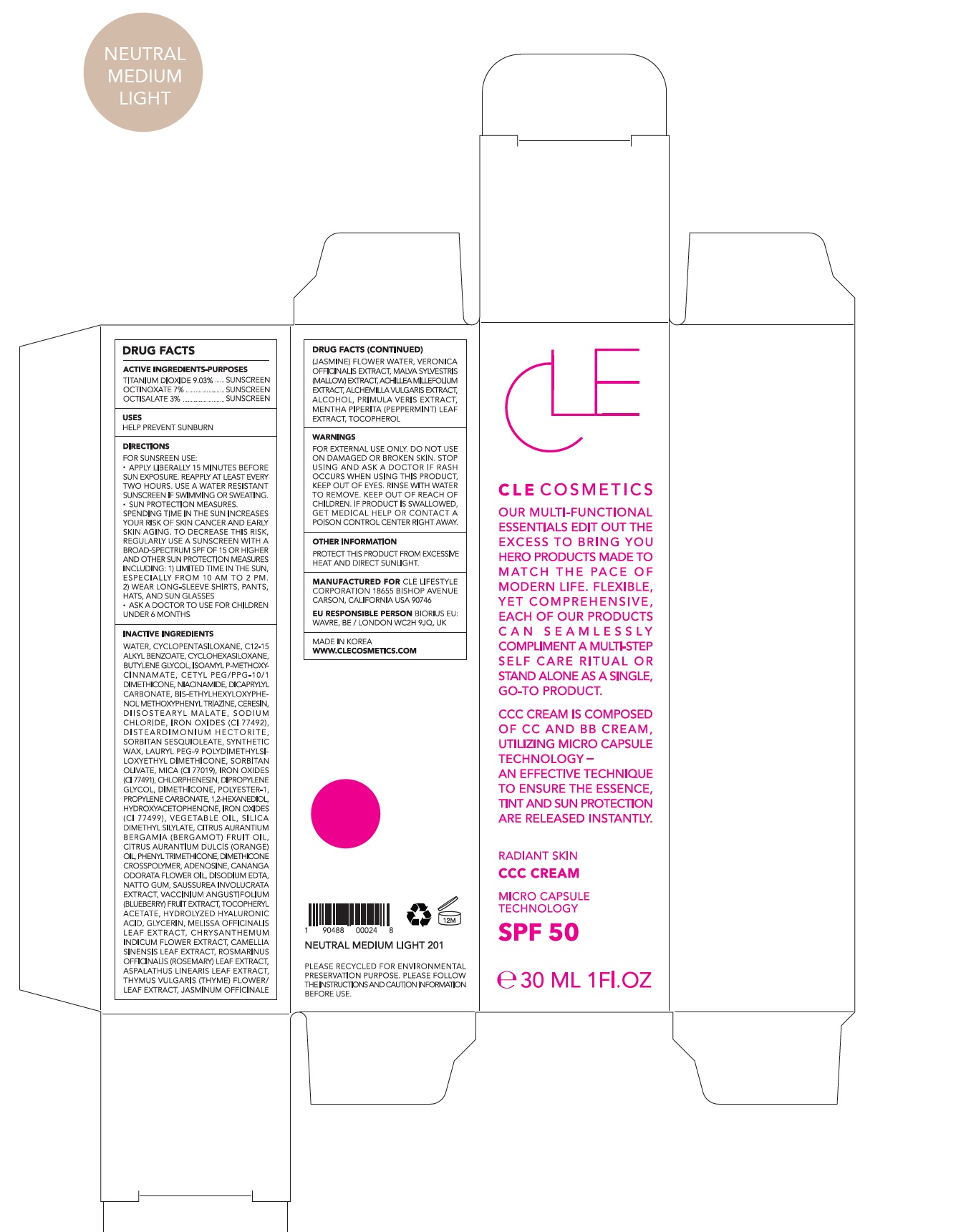 DRUG LABEL: CLE CCC Neutral Medium Light
NDC: 69231-029 | Form: CREAM
Manufacturer: KW ABSC, INC.
Category: otc | Type: HUMAN OTC DRUG LABEL
Date: 20241219

ACTIVE INGREDIENTS: OCTINOXATE 2.1 mg/30 mL; OCTISALATE 0.9 mg/30 mL; TITANIUM DIOXIDE 2.7096 mg/30 mL
INACTIVE INGREDIENTS: WATER; CYCLOMETHICONE 5; ALKYL (C12-15) BENZOATE; CYCLOMETHICONE 6; BUTYLENE GLYCOL; AMILOXATE; CETYL PEG/PPG-10/1 DIMETHICONE (HLB 2); NIACINAMIDE; DICAPRYLYL CARBONATE; BEMOTRIZINOL; CERESIN; DIISOSTEARYL MALATE; SODIUM CHLORIDE; FERRIC OXIDE YELLOW; DISTEARDIMONIUM HECTORITE; SORBITAN SESQUIOLEATE; SYNTHETIC WAX (1200 MW); LAURYL PEG-9 POLYDIMETHYLSILOXYETHYL DIMETHICONE; SORBITAN OLIVATE; MICA; FERRIC OXIDE RED; CHLORPHENESIN; DIPROPYLENE GLYCOL; DIMETHICONE; POLYESTER-10; PROPYLENE CARBONATE; 1,2-HEXANEDIOL; HYDROXYACETOPHENONE; FERROSOFERRIC OXIDE; CORN OIL; SILICA DIMETHYL SILYLATE; BERGAMOT OIL; ORANGE OIL; PHENYL TRIMETHICONE; DIMETHICONE CROSSPOLYMER (450000 MPA.S AT 12% IN CYCLOPENTASILOXANE); ADENOSINE; CANANGA OIL; EDETATE DISODIUM ANHYDROUS

69231-029_CLE CCC Neutral Medium Light

ACTIVE INGREDIENT

Titanium Dioxide 9.03%

Ethylhexyl Methoxycinnamate 7.00%

Ethylhexyl Salicylate 3.00%

PURPOSE

Sunscreen

INDICATIONS AND USAGE

Helps prevent sunburn

DOSAGE AND ADMINISTRATION

Apply liberally 15 minutes before sun exposure. Reapply at least every two hours

Sun protection measures. Spending time in the sun increases your risk of skin cancer and early skin aging. To decrease this risk, regularly use a sunscreen with a broad spectrum SPF of 15 of higher and other sun protection measures including: 1) Limited time in the sun, especially from 10 am to 2 pm. 2) Wear long-sleeve shirts, pants, hats, and sunglasses
Ask a doctor to use for children under 6 months

WARNINGS

For external use only.
Do not use on damaged or broken skin.
When using this product, keep out of eyes. Rinse with water to remove.
Stop using and ask a doctor if rash occurs.

KEEP OUT OF REACH OF CHILDREN

Keep out of reach of the children. If product is swallowed, get medical help or contact a poison control center right away.

INACTIVE INGREDIENT

Water, Cyclopentasiloxane, C12-15 Alkyl Benzoate, Cyclohexasiloxane, Butylene Glycol, Isoamyl p-Methoxycinnamate, Cetyl PEG/PPG-10/1 Dimethicone, Niacinamide, Dicaprylyl Carbonate, Bis-Ethylhexyloxyphenol Methoxyphenyl Triazine, Ceresin, Diisostearyl Malate, Sodium Chloride, Iron Oxides (CI 77492), Disteardimonium Hectorite, Sorbitan Sesquioleate, Synthetic Wax, Lauryl PEG-9 Polydimethylsiloxyethyl Dimethicone, Sorbitan Olivate, Mica (CI 77019), Iron Oxides (CI 77491), Chlorphenesin, Dipropylene Glycol, Dimethicone, Polyester-1, Propylene Carbonate, 1,2-Hexanediol, Hydroxyacetophenone, Iron Oxides (CI 77499), Vegetable Oil, Silica Dimethyl Silylate, Citrus Aurantium Bergamia (Bergamot) Fruit Oil, Citrus Aurantium Dulcis (Orange) Oil, Phenyl Trimethicone, Dimethicone Crosspolymer, Adenosine, Cananga Odorata Flower Oil, Disodium EDTA, Natto Gum, Saussurea Involucrata Extract, Bambusa Vulgaris Leaf/Stem Extract, Vaccinium Angustifolium (Blueberry) Fruit Extract, Cocos Nucifera (Coconut) Oil, Tocopheryl Acetate, Hydrolyzed Hyaluronic Acid, Glycerin, Melissa Officinalis Leaf Extract, Chrysanthemum Indicum Flower Extract, Camellia Sinensis Leaf Extract, Rosmarinus Officinalis (Rosemary) Leaf Extract, Aspalathus Linearis Leaf Extract, Thymus Vulgaris (Thyme) Flower/Leaf Extract, Jasminum Officinale (Jasmine) Flower Water, Veronica Officinalis Extract, Malva Sylvestris (Mallow) Extract, Achillea Millefolium Extract, Alchemilla Vulgaris Extract, Alcohol, Primula Veris Extract, Mentha Piperita (Peppermint) Leaf Extract, Tocopherol